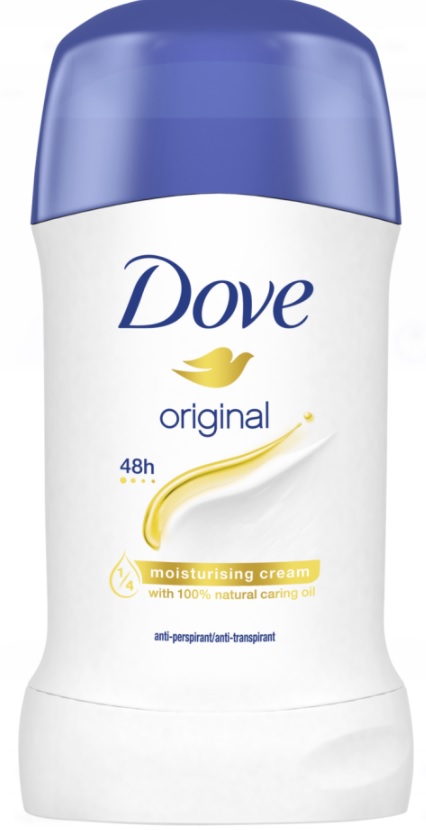 DRUG LABEL: DOVE Antiperspirant
NDC: 51769-089 | Form: STICK
Manufacturer: All Natural Dynamics	
Category: otc | Type: HUMAN OTC DRUG LABEL
Date: 20220317

ACTIVE INGREDIENTS: ALUMINUM ZIRCONIUM TETRACHLOROHYDREX GLY 15.2 g/100 g
INACTIVE INGREDIENTS: BENZYL ALCOHOL; BENZYL BENZOATE; BENZYL SALICYLATE; BUTYLPHENYL METHYLPROPIONAL; .BETA.-CITRONELLOL, (R)-; GERANIOL; CYCLOMETHICONE 5; ALKYL (C12-15) BENZOATE; PPG-14 BUTYL ETHER; HYDROGENATED CASTOR OIL; HIGH DENSITY POLYETHYLENE; .ALPHA.-TOCOPHEROL ACETATE; ACONITIC ACID; ISOMETHYL-.ALPHA.-IONONE; .ALPHA.-HEXYLCINNAMALDEHYDE; ISOEUGENOL; LINALOOL, (+/-)-; HYDROXYCITRONELLAL; LIMONENE, (+)-; BUTYLATED HYDROXYTOLUENE; STEARYL ALCOHOL; DIMETHICONE; SUNFLOWER OIL; STEARETH-100

Dove Original Antiperspirant Deodorant Stick

Active Ingredient

Aluminum Zirconium Tetrachlorohydrex GLY (15.2%)

Purpose

anti-perspirant

Uses

reduces underarm wetness

Warnings

· For External Use Only.

· Do not use

on broken skin.

· Ask a doctor before use if you have

kidney disease.

· Stop use if

rash or irritation occurs.

· Keep out of reach of children.

If swallowed, get medical help or contact a Poison Control Center right away.

Directions

apply to underarms only

Inactive ingredients:

Cyclopentasiloxane, Stearyl Alcohol, C12-15 Alkyl Benzoate, PPG-14 Butyl Ether, Hydrogenated Castor Oil, Parfum, Dimethicone, Polyethylene, Helianthus Annuus Seed Oil, Steareth-100, BHT, Alpha-Isomethyl Ionone, Benzyl Benzoate, Benzyl Salicylate, Butylphenyl Methylpropional, Citronellol, Geraniol, Hexyl Cinnamal, Hydroxycitronellal, Linalool

Questions?

Call 1-800-761-3683